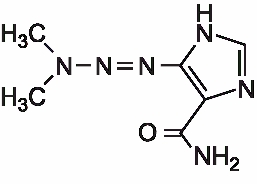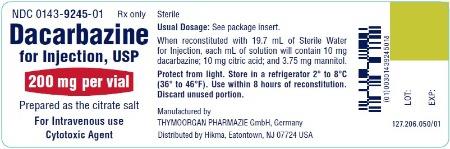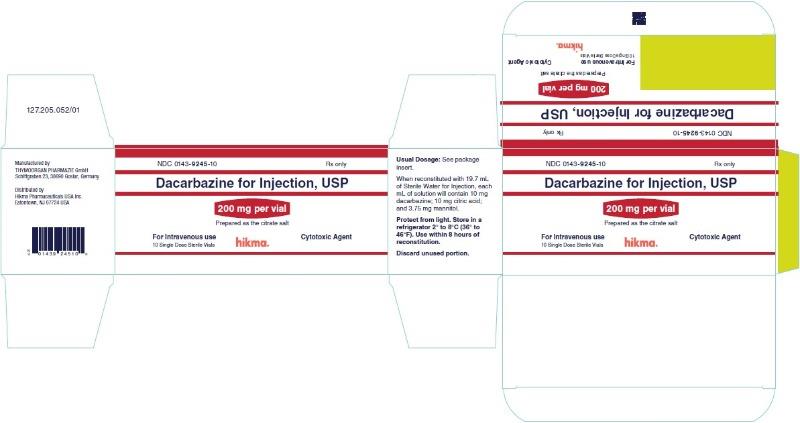 DRUG LABEL: Dacarbazine
NDC: 0143-9245 | Form: INJECTION, POWDER, LYOPHILIZED, FOR SOLUTION
Manufacturer: Hikma Pharmaceuticals USA Inc.
Category: prescription | Type: HUMAN PRESCRIPTION DRUG LABEL
Date: 20250922

ACTIVE INGREDIENTS: DACARBAZINE 200 mg/1 1
INACTIVE INGREDIENTS: MANNITOL; ANHYDROUS CITRIC ACID

Dacarbazine for Injection, USP

Rx only

WARNING

It is recommended that dacarbazine be administered under the supervision of a qualified physician experienced in the use of cancer chemotherapeutic agents.

- 1.Hemopoietic depression is the most common toxicity with dacarbazine (see WARNINGS).
- 2.Hepatic necrosis has been reported (see WARNINGS).
- 3.Studies have demonstrated this agent to have a carcinogenic and teratogenic effect when used in animals.
- 4.In treatment of each patient, the physician must weigh carefully the possibility of achieving therapeutic benefit against the risk of toxicity.

Boxed Warning

WARNING

It is recommended that dacarbazine be administered under the supervision of a qualified physician experienced in the use of cancer chemotherapeutic agents.

1. Hemopoietic depression is the most common toxicity with dacarbazine (see WARNINGS).
2. Hepatic necrosis has been reported (see WARNINGS).
3. Studies have demonstrated this agent to have a carcinogenic and teratogenic effect when used in animals.
4. In treatment of each patient, the physician must weigh carefully the possibility of achieving therapeutic benefit against the risk of toxicity.

DESCRIPTION

Dacarbazine for Injection, USP is a colorless to an ivory colored solid which is light sensitive. Each vial contains 200 mg of dacarbazine (the active ingredient), anhydrous citric acid and mannitol. Dacarbazine is reconstituted and administered intravenously (pH 3.0 to 4.0). Dacarbazine is an anticancer agent. Chemically, dacarbazine is 5-(3,3-Dimethyl-1-triazeno)imidazole-4-carboxamide with the following structural formula:

C6H10N6O M.W. = 182.19

CLINICAL PHARMACOLOGY

After intravenous administration of dacarbazine, the volume of distribution exceeds total body water content suggesting localization in some body tissue, probably the liver. Its disappearance from the plasma is biphasic with initial half-life of 19 minutes and a terminal half-life of 5 hours. In a patient with renal and hepatic dysfunctions, the half-lives were lengthened to 55 minutes and 7.2 hours. The average cumulative excretion of unchanged dacarbazine in the urine is 40% of the injected dose in 6 hours. Dacarbazine is subject to renal tubular secretion rather than glomerular filtration. At therapeutic concentrations dacarbazine is not appreciably bound to human plasma protein.

In man, dacarbazine is extensively degraded. Besides unchanged dacarbazine, 5-aminoimidazole-4-carboxamide (AIC) is a major metabolite of dacarbazine excreted in the urine. AIC is not derived endogenously but from the injected dacarbazine, because the administration of radioactive dacarbazine labeled with ^14C in the imidazole portion of the molecule (dacarbazine-2-^14C) gives rise to AIC-2-^14C.

Although the exact mechanism of action of dacarbazine is not known, three hypotheses have been offered:

1.inhibition of DNA synthesis by acting as a purine analog

2.action as an alkylating agent

3.interaction with SH groups

INDICATIONS AND USAGE

Dacarbazine for Injection, USP is indicated in the treatment of metastatic malignant melanoma. In addition, dacarbazine is also indicated for Hodgkin's disease as a second-line therapy when used in combination with other effective agents.

CONTRAINDICATIONS

Dacarbazine is contraindicated in patients who have demonstrated a hypersensitivity to it in the past.

WARNINGS

Hemopoietic depression is the most common toxicity with dacarbazine and involves primarily the leukocytes and platelets, although, anemia may sometimes occur. Leukopenia and thrombocytopenia may be severe enough to cause death. The possible bone marrow depression requires careful monitoring of white blood cells, red blood cells, and platelet levels. Hemopoietic toxicity may warrant temporary suspension or cessation of therapy with dacarbazine.

Hepatic toxicity accompanied by hepatic vein thrombosis and hepatocellular necrosis resulting in death, has been reported. The incidence of such reactions has been low; approximately 0.01% of patients treated. This toxicity has been observed mostly when dacarbazine has been administered concomitantly with other anti-neoplastic drugs; however, it has also been reported in some patients treated with dacarbazine alone.

Anaphylaxis can occur following the administration of dacarbazine.

PRECAUTIONS

Hospitalization is not always necessary but adequate laboratory study capability must be available. Extravasation of the drug subcutaneously during intravenous administration may result in tissue damage and severe pain. Local pain, burning sensation, and irritation at the site of injection may be relieved by locally applied hot packs.

Carcinogenicity of dacarbazine was studied in rats and mice. Proliferative endocardial lesions, including fibrosarcomas and sarcomas were induced by dacarbazine in rats. In mice, administration of dacarbazine resulted in the induction of angiosarcomas of the spleen.

Pregnancy

Teratogenic effects; Pregnancy Category C

Dacarbazine has been shown to be teratogenic in rats when given in doses 20 times the human daily dose on day 12 of gestation. Dacarbazine when administered in 10 times the human daily dose to male rats (twice weekly for 9 weeks) did not affect the male libido, although female rats mated to male rats had higher incidence of resorptions than controls. In rabbits, dacarbazine daily dose 7 times the human daily dose given on Days 6 to 15 of gestation resulted in fetal skeletal anomalies. There are no adequate and well-controlled studies in pregnant women. Dacarbazine should be used during pregnancy only if the potential benefit justifies the potential risk to the fetus.

It is not known whether this drug is excreted in human milk. Because many drugs are excreted in human milk and because of the potential for tumorigenicity shown for dacarbazine in animal studies, a decision should be made whether to discontinue nursing or to discontinue the drug, taking into account the importance of the drug to the mother.

ADVERSE REACTIONS

Symptoms of anorexia, nausea, and vomiting are the most frequently noted of all toxic reactions. Over 90% of patients are affected with the initial few doses. The vomiting lasts 1 to 12 hours and is incompletely and unpredictably palliated with phenobarbital and/or prochlorperazine. Rarely, intractable nausea and vomiting have necessitated discontinuance of therapy with dacarbazine. Rarely, dacarbazine has caused diarrhea. Some helpful suggestions include restricting the patient’s oral intake of food for 4 to 6 hours prior to treatment. The rapid toleration of these symptoms suggests that a central nervous system mechanism may be involved, and usually these symptoms subside after the first 1 or 2 days.

There are a number of minor toxicities that are infrequently noted. Patients have experienced an influenza-like syndrome of fever to 39°C, myalgias and malaise. These symptoms occur usually after large single doses, may last for several days, and they may occur with successive treatments.

Alopecia has been noted as has facial flushing and facial paresthesia. There have been few reports of significant liver or renal function test abnormalities in man. However, these abnormalities have been observed more frequently in animal studies.

Erythematous and urticarial rashes have been observed infrequently after administration of dacarbazine. Rarely, photosensitivity reactions may occur.

OVERDOSAGE

Give supportive treatment and monitor blood cell counts.

DOSAGE AND ADMINISTRATION

Malignant Melanoma

The recommended dosage is 2 to 4.5 mg/kg/day for 10 days. Treatment may be repeated at 4 week intervals.

An alternate recommended dosage is 250 mg/square meter body surface/day I.V. for 5 days. Treatment may be repeated every 3 weeks.

Hodgkin's Disease

The recommended dosage of dacarbazine in the treatment of Hodgkin's disease is 150 mg/square meter body surface/day for 5 days, in combination with other effective drugs. Treatment may be repeated every 4 weeks. An alternative recommended dosage is 375 mg/square meter body surface on day 1, in combination with other effective drugs, to be repeated every 15 days.

Dacarbazine 200 mg/vial is reconstituted with 19.7 mL of Sterile Water for Injection. The resulting solution contains 10 mg/mL of dacarbazine having a pH of 3.0 to 4.0. The calculated dose of the resulting solution is drawn into a syringe and administered only intravenously.

The reconstituted solution may be further diluted with 5% dextrose injection, or sodium chloride injection, and administered as an intravenous infusion.

After reconstitution and prior to use, the solution in the vial may be stored at 4°C for up to 72 hours or at normal room conditions (temperature and light) for up to 8 hours. If the reconstituted solution is further diluted in 5% dextrose injection or sodium chloride injection, the resulting solution may be stored at 4°C for up to 24 hours or at normal room conditions for up to 8 hours.

Procedures for proper handling and disposal of anticancer drugs should be considered. Several guidelines on this subject have been published.^1-7 There is no general agreement that all of the procedures recommended in the guidelines are necessary or appropriate.

Parenteral drug products should be inspected visually for particulate matter or discoloration prior to administration whenever solution and container permit.

HOW SUPPLIED

Dacarbazine for Injection, USP is supplied as follows:

NDC 0143-9245-10 200 mg/vial of sterile dacarbazine in boxes of 10.

Store in a refrigerator 2° to 8°C (36° to 46°F).

To report SUSPECTED ADVERSE REACTIONS, contact Hikma Pharmaceuticals USA Inc. at 1-877-845-0689, or the FDA at 1-800-FDA-1088 or www.fda.gov/medwatch.

For Product Inquiry call 1-877-845-0689.

REFERENCES

1.Recommendations for the Safe Handling of Parenteral Antineoplastic Drugs. NIH Publication No. 83-2621. For sale by the Superintendent of Documents, U.S. Government Printing Office, Washington, D.C. 20402.

2.AMA Council Report. Guidelines for Handling Parenteral Antineoplastics. JAMA, March 15, 1985.

3.National Study Commission on Cytotoxic Exposure Recommendations for Handling Cytotoxic Agents. Available from Louis P. Jeffrey, Sc. D., Director of Pharmacy Services, Rhode Island Hospital, 593 Eddy Street. Providence. Rhode Island 02902.

4.Clinical Oncological Society of Australia, Guidelines and recommendations for safe handling of antineoplastic agents. Med. J. Australia 1: 426-428, 1983.

5.Jones, R. B.. et al.: Safe handling of chemotherapeutic agents: A report from the Mount Sinai Medical Center. Ca-A Cancer Journal for Clinicians Sept./Oct., 258-263.1983.

6.American Society of Hospital Pharmacists technical assistance bulletin on handling cytotoxic drugs in hospitals. Am. J.Hosp. Pharm, 42: 131-137, 1985.

7.Controlling Occupational Exposure to Hazardous Drugs. (OSHA Work-Practice Guidelines). Am J Health-Syst Pharm, 53: 1669-1685, 1996.

Manufactured by
THYMOORGAN PHARMAZIE GmbH,
Schiffgraben 23, 38690 Goslar, Germany

Distributed by
Hikma Pharmaceuticals USA Inc.
Eatontown, NJ 07724 USA

Revised March 2020

127.207.024/01

PRINCIPAL DISPLAY PANEL

NDC 0143-9245-01 Rx only
Dacarbazine
for Injection, USP
200 mg per vial
Prepared as the citrate salt
For Intravenous use
Cytotoxic Agent

NDC 0143-9245-10 Rx only
Dacarbazine for Injection, USP
200 mg per vial
Prepared as the citrate salt
For Intravenous use
Cytotoxic Agent
10 Single Dose Sterile Vials